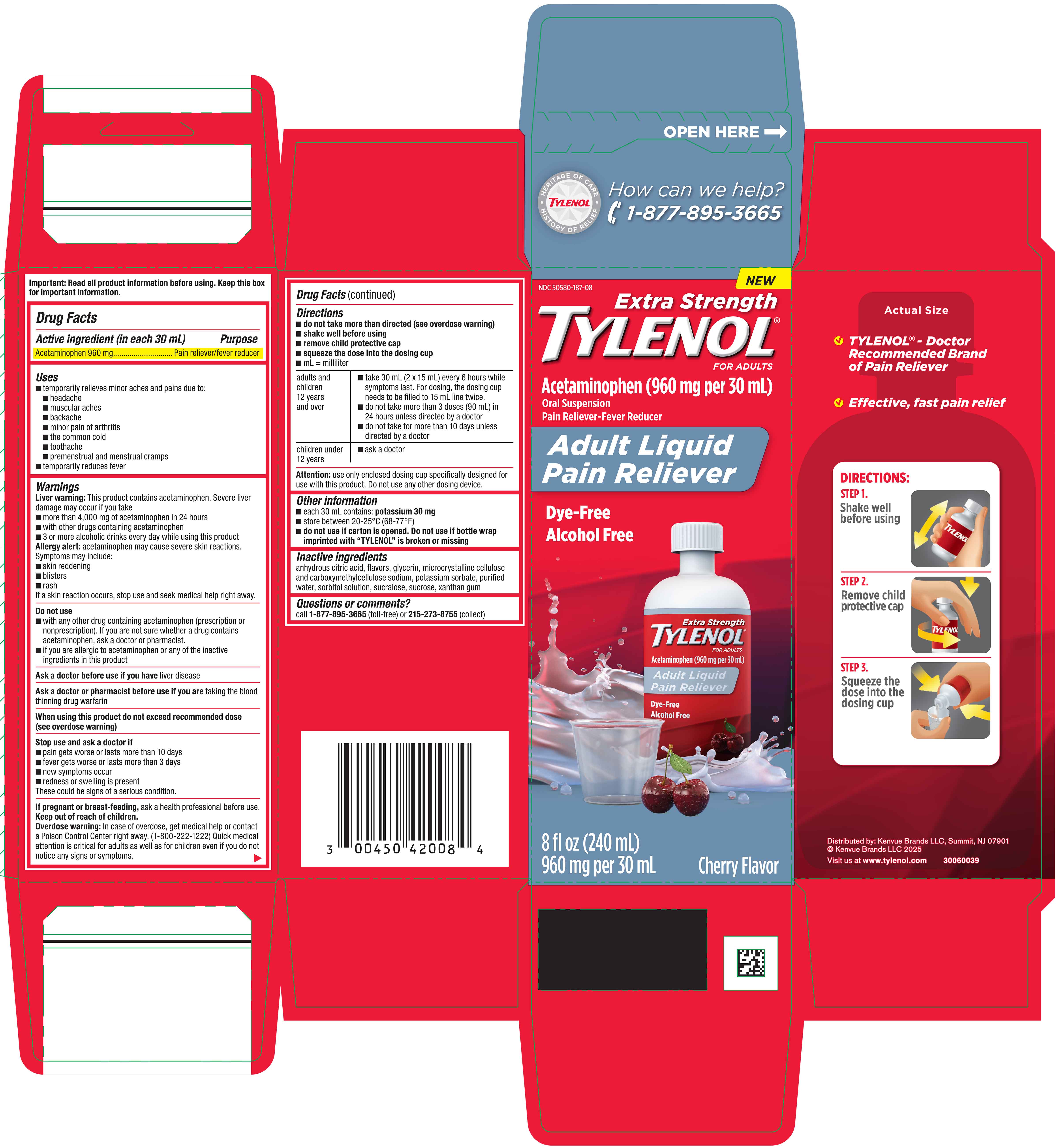 DRUG LABEL: TYLENOL Extra Strength
NDC: 50580-187 | Form: SUSPENSION
Manufacturer: Kenvue Brands LLC
Category: otc | Type: HUMAN OTC DRUG LABEL
Date: 20251105

ACTIVE INGREDIENTS: ACETAMINOPHEN 960 mg/30 mL
INACTIVE INGREDIENTS: SUCROSE; ANHYDROUS CITRIC ACID; POTASSIUM SORBATE; GLYCERIN; XANTHAN GUM; MICROCRYSTALLINE CELLULOSE; CARBOXYMETHYLCELLULOSE SODIUM; WATER; SORBITOL SOLUTION; SUCRALOSE

TYLENOL® Extra Strength

Drug Facts

Active ingredient (in each 30 mL)

Acetaminophen 960 mg

Purpose

Pain reliever/fever reducer

Uses

■ temporarily relieves minor aches and pains due to:

- headache
- muscular aches
- backache
- minor pain of arthritis
- the common cold
- toothache
- premenstrual and menstrual cramps

■ temporarily reduces fever

Warnings

Liver warning

This product contains acetaminophen. Severe liver damage may occur if you take
■ more than 4,000 mg of acetaminophen in 24 hours
■ with other drugs containing acetaminophen
■ 3 or more alcoholic drinks every day while using this product

Allergy alert

Acetaminophen may cause severe skin reactions.
Symptoms may include:
■ skin reddening
■ blisters
■ rash
If a skin reaction occurs, stop use and seek medical help right away.

Do not use

■ with any other drug containing acetaminophen (prescription or nonprescription). If you are not sure whether a drug contains
acetaminophen, ask a doctor or pharmacist.
■ if you are allergic to acetaminophen or any of the inactive ingredients in this product

Ask a doctor before use if you have liver disease

Ask a doctor or pharmacist before use if you are taking the blood thinning drug warfarin

When using this product do not exceed recommended dose (see overdose warning)

Stop use and ask a doctor if

■ pain gets worse or lasts more than 10 days
■ fever gets worse or lasts more than 3 days
■ new symptoms occur
■ redness or swelling is present
These could be signs of a serious condition.

If pregnant or breast-feeding, ask a health professional before use.

Keep out of reach of children.

Overdose warning

In case of overdose, get medical help or contact a Poison Control Center right away. (1-800-222-1222) Quick medical attention is critical for adults as well as for children even if you do not notice any signs or symptoms.

Directions

■ do not take more than directed (see overdose warning)
■ shake well before using
■ remove child protective cap
■ squeeze the dose into the dosing cup
■ mL = milliliter

adults and children 12 years and over | ■ take 30 mL (2 x 15 mL) every 6 hours while symptoms last. For dosing, the dosing cup needs to be filled to 15 mL line twice. ■ do not take more than 3 doses (90 mL) in 24 hours unless directed by a doctor ■ do not take for more than 10 days unless directed by a doctor
children under 12 years | ■ ask a doctor

Attention: use only enclosed dosing cup specifically designed for use with this product. Do not use any other dosing device.

Other information

■ each 30 mL contains: potassium 30 mg
■ store between 20-25°C (68-77°F)
■ do not use if carton is opened. Do not use if bottle wrap imprinted with “TYLENOL” is broken or missing

Inactive ingredients

anhydrous citric acid, flavors, glycerin, microcrystalline cellulose and carboxymethylcellulose sodium, potassium sorbate, purified water, sorbitol solution, sucralose, sucrose, xanthan gum

Questions or comments?

Call 1-877-895-3665 (toll-free) or 215-273-8755 (collect)

PRINCIPAL DISPLAY PANEL

NDC 50580-187-08

NEW

Extra Strength
TYLENOL®

FOR ADULTS

Acetaminophen (960 mg per 30 mL)
Oral Suspension

Pain Reliever-Fever Reducer

Adult Liquid
Pain Reliever

Dye-Free
Alcohol Free
8 fl oz (240 mL)

960 mg per 30 mL
Cherry Flavor